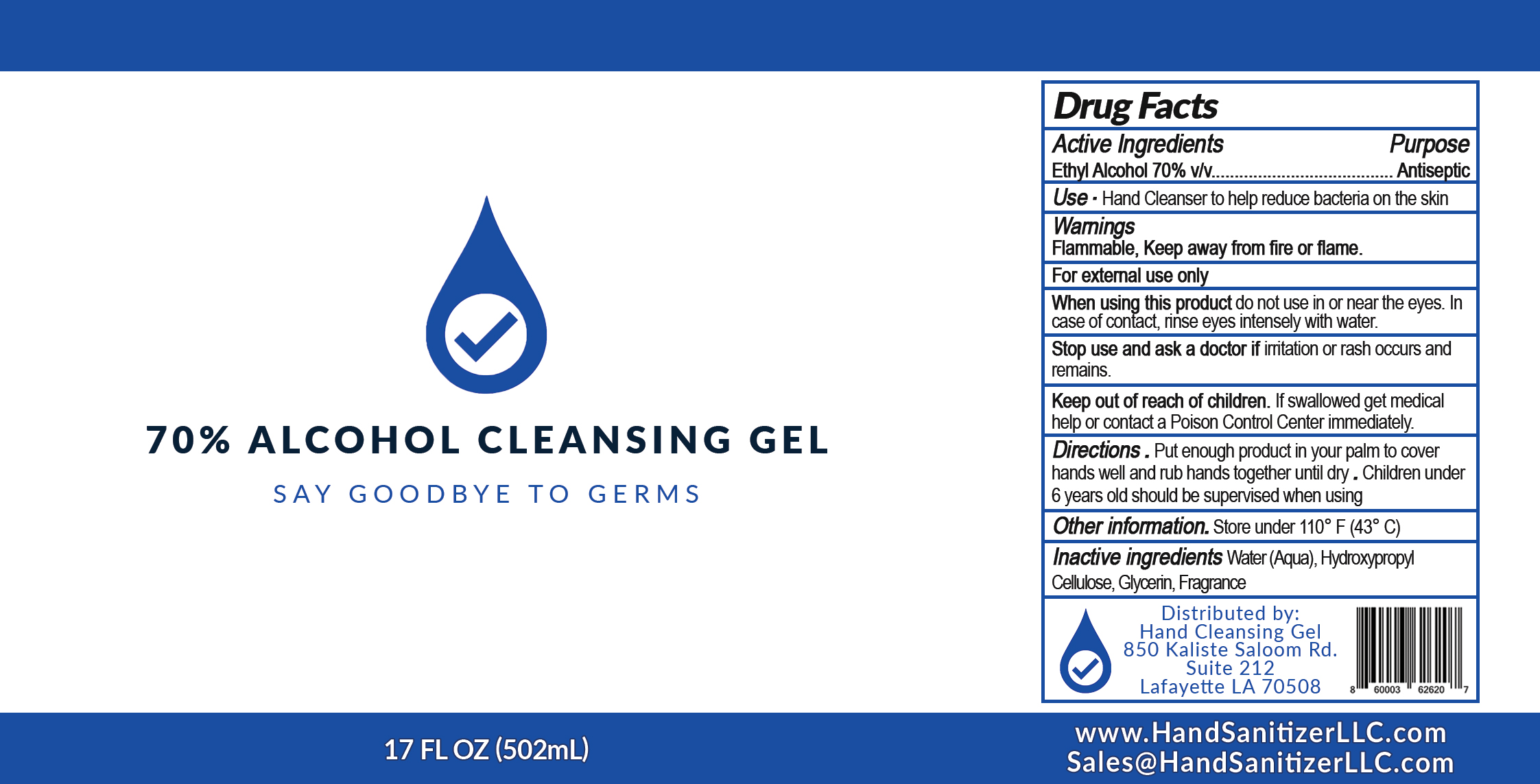 DRUG LABEL: Hand Cleansing Gel
NDC: 76701-700 | Form: GEL
Manufacturer: Hand Sanitizer LLC
Category: otc | Type: HUMAN OTC DRUG LABEL
Date: 20200423

ACTIVE INGREDIENTS: ALCOHOL 0.7 mL/1 mL
INACTIVE INGREDIENTS: WATER; GLYCERIN; HYDROXYPROPYL CELLULOSE, UNSPECIFIED

ACTIVE INGREDIENT

Ethyl Alcohol 70%

PURPOSE

Antiseptic

INDICATIONS AND USAGE

Hand Cleanser to help reduce bacteria on the skin.

WARNINGS

Flammable, Keep away from fire or flame.

For External use only

When using this product do not use in or near the eys. In case of contact, rinse eyes intensely with water.

Stop Use and ask a doctor if irritation or rash occurs and remains.

Keep out of reach of children. If swallowed get medical help or contact a Poison Control Center immediately.

DOSAGE AND ADMINISTRATION

Put enough product in your palm to cover hands well and rub hands together until dry. Children under 6 years old should be supervised when using.

OTHER SAFETY INFORMATION

Store under 110°F (43°C)

INACTIVE INGREDIENT

Water (Aqua), Hydroxypropyl Cellulose, Glycerin, Fragrance

PACKAGE LABEL

70% Alcohol Cleansing Gel